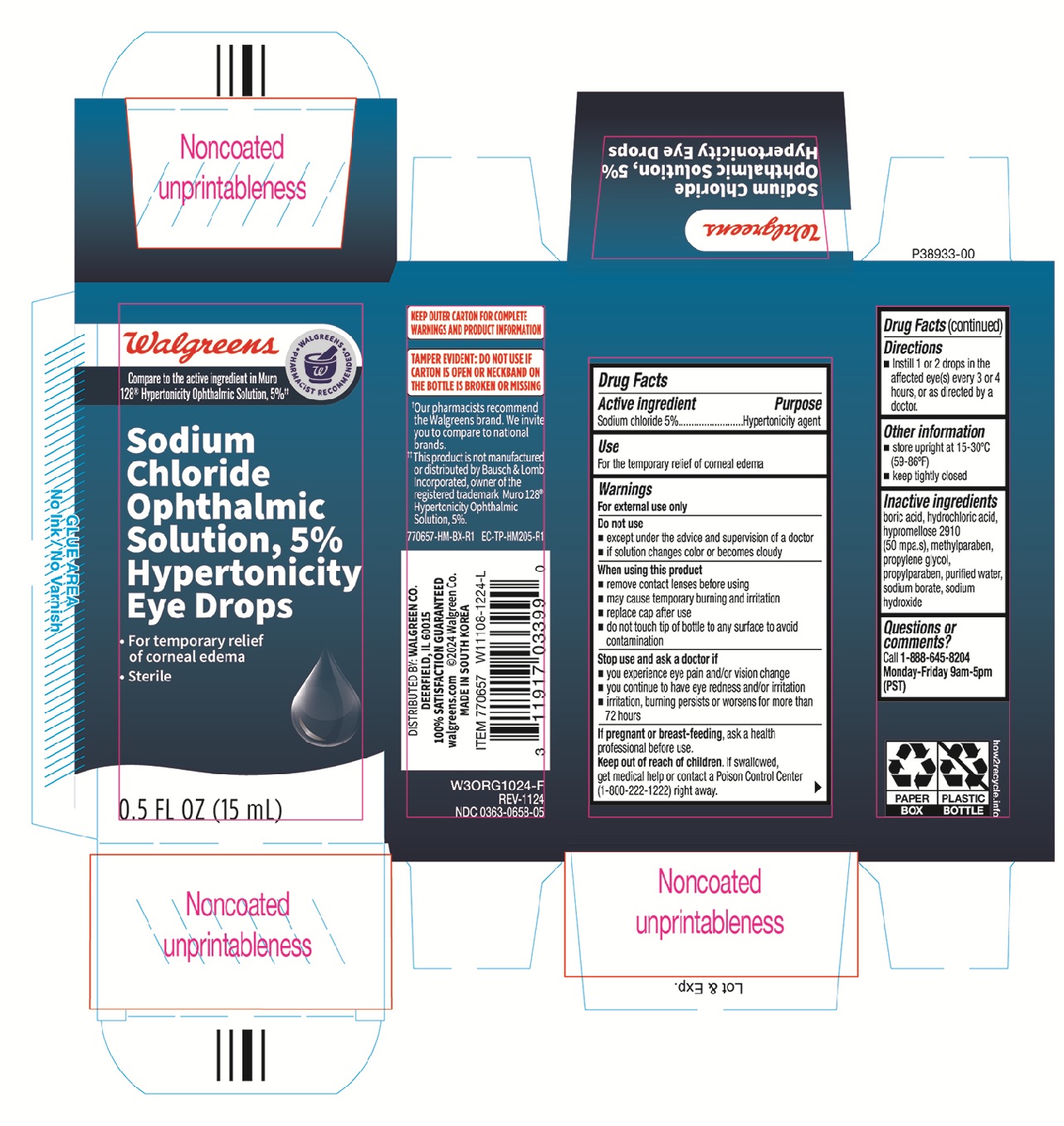 DRUG LABEL: Walgreens
NDC: 0363-0658 | Form: SOLUTION/ DROPS
Manufacturer: Walgreen Company
Category: otc | Type: HUMAN OTC DRUG LABEL
Date: 20251017

ACTIVE INGREDIENTS: SODIUM CHLORIDE 50 mg/1 mL
INACTIVE INGREDIENTS: HYDROCHLORIC ACID; BORIC ACID; PROPYLPARABEN; WATER; SODIUM BORATE; SODIUM HYDROXIDE; HYPROMELLOSE 2910 (50 MPA.S); METHYLPARABEN

Walgreens Sodium Chloride Ophthalmic Solution 5% Hypertonicity Eye Drops 0.5oz 770657 (NBE Muro128)

Active ingredient Purpose

Sodium chloride 5%.............................Hypertonicity agent

Use

For the temporary relief of corneal edema

When using this product

- remove contact lenses before using
- may cause temporary burning and irritation
- replace cap after use
- do not touch tip of bottle to any surface to avoid contamination

Stop use and ask a doctor if

- you experience eye pain and/or vision change
- you continue to have eye redness and or irritation
- irritation, burning persits or worsens for more than 72 hours

PREGNANCY OR BREAST FEEDING

If pregnant or breast-feeding, ask a health professional before use.

Keep out of reach of children. If swallowed, get medical help or contact a Poison Control Center (1-800-222-1222) right away.

Directions

- Instill 1 or 2 drops in the affected eye(s) every 3 or 4 hours, or as directed by a doctor.

Other information

- store upright at 15-30°C (59-86°F)
- keep tightly closed

Inactive ingredients

boric acid, hydrochloric acid, hypromellose 2910 (50 mpa.s), methylparaben, propylene glycol, propylparaben, purified water, sodium borate, sodium hydroxide

DOSAGE AND ADMINISTRATION

Distributed by:

Walgreen Co.

Deerfield, IL 60015

Made in South Korea